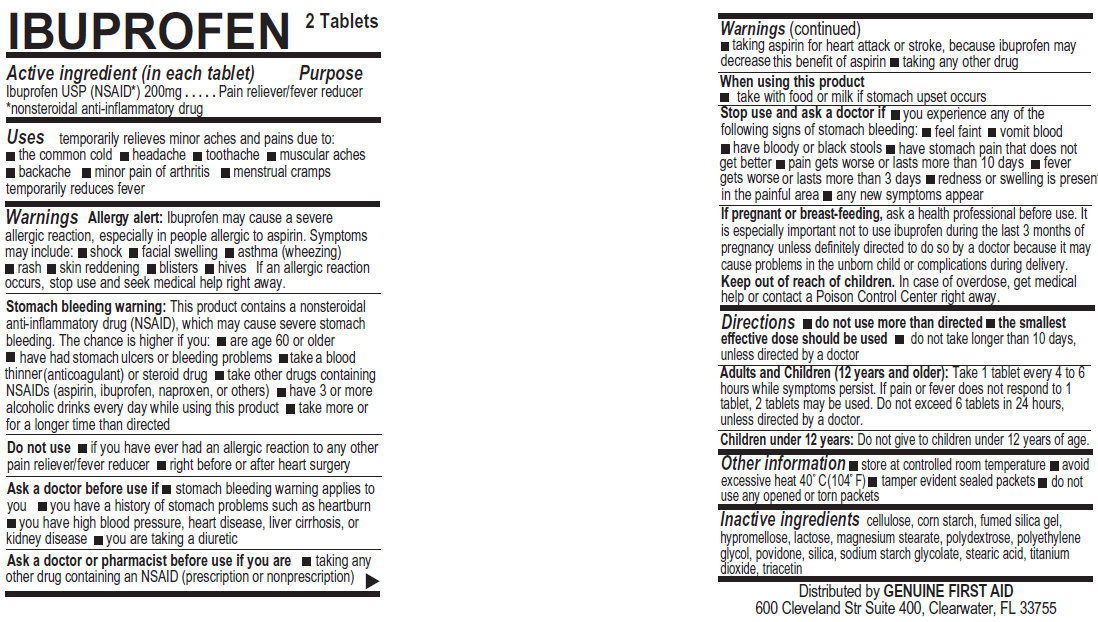 DRUG LABEL: Ibuprofen

NDC: 52124-0009 | Form: TABLET
Manufacturer: Genuine First Aid LLC
Category: otc | Type: HUMAN OTC DRUG LABEL
Date: 20171230

ACTIVE INGREDIENTS: IBUPROFEN 200 mg/1 1
INACTIVE INGREDIENTS: POLYETHYLENE GLYCOL; POVIDONE; SILICON DIOXIDE; STEARIC ACID; TITANIUM DIOXIDE; TRIACETIN; POWDERED CELLULOSE; STARCH, CORN; HYPROMELLOSES; LACTOSE; MAGNESIUM STEARATE; POLYDEXTROSE

Ibuprofen, 200 mg

Active Ingredient (in each tablet)

Ibuprofen USP (NSAID*) 200mg
*nonsteroidal anti-inflammatory drug

Purpose

Pain reliever/fever reducer

Uses

temporarily relieves minor aches and pains due to:
the common cold
headache
toothache
muscular aches
backache
minor pain of arthritis
menstrual cramps temporarily reduces fever

Warnings

Allergy alert: Ibuprofen may cause a severe allergic reaction, especially in people allergic to aspirin. Symptoms may include: shock, facial swelling, asthma (wheezing) rash, skin reddening, blisters, hives If an allergic reaction occurs, stop use and seek medical help right away.
Stomach bleeding warning: This product contains a nonsteroidal anti-inflammatory drug (NSAID), which may cause severe stomach bleeding. The chance is higher if you: are age 60 or older, have had stomach ulcers or bleeding problems, take a blood thinner (anticoagulant) or steroid drug, take other drugs containing NSAIDs (aspirin, ibuprofen, naproxen, or others), have 3 or more alcoholic drinks every day while using this product, take more or for a longer time than directed

Do not use if you have ever had an allergic reaction to any other pain reliever/fever reducer, right before or after heart surgery.

Ask a doctor before use if stomach bleeding warning applies to you; you have a history of stomach problems such as heartburn; you have a high blood pressure, heart disease, liver cirrhosis, or kidney disease; you are taking a diuretic

Ask a doctor before use if you are:

taking any other drug containing NSAID (prescription or nonprescription); taking aspirin for heart attack or stroke, because Ibuprofen may decrease this benefit of aspirin; taking any other drug

When using this product

take with food or milk if stomach upset occurs

Stop use and ask a doctor if

you experience any of the following signs of stomach bleeding; feel faint; vomit blood; have bloody or black stools; have stomach pain that does get better; pain gets worse or lasts more than 10 days; fever gets worse or lasts more than 3 days; redness or swelling is present in the painful area; any new symptoms appear

PREGNANCY OR BREAST FEEDING

If pregnant or breast-feeding, ask a health professional before use. It is especially important not to use ibuprofen during the last 3 months of pregnancy unless definitely directed to do so by a doctor because it may cause problems in the unborn child or complications during delivery.

Keep out of reach of children. In case of overdose, get medical help or contact a Poison Control Center right away.

Directions

do not use more than directed; the smallest effective dose should be used; do not take longer than 10 days, unless directed by a doctor.
Adults and Children (12 years and older): Take 1 tablet every 4 to 6 hours while symptoms persist. If pain or fever does not respond to 1 tablet, 2 tablets may be used. Do not exceed 6 tablets in 24 hours, unless directed by a doctor.
Children under 12 years: Do not give to children under 12 years of age.

Other information

Store at controlled room temperature; avoid excessive heat 40 degree Celsius (104 degree Fahrenheit); tamper evident sealed packets; do not use any opened or torn packets

Inactive Ingredients

cellulose, corn starch, fumed silica gel, hypromellose, lactose, magnesium stearate, polydextrose, polyethylene glycol, povidone, silica, sodium starch glycolate, stearic acid, titanium dioxide, triacetin.

DESCRIPTION

Distributed by GENUINE FIRST AID
600 Cleveland Str Suite 400, Clearwater, FL 33755

PACKAGE LABEL

IBUPROFEN 2 Tablets